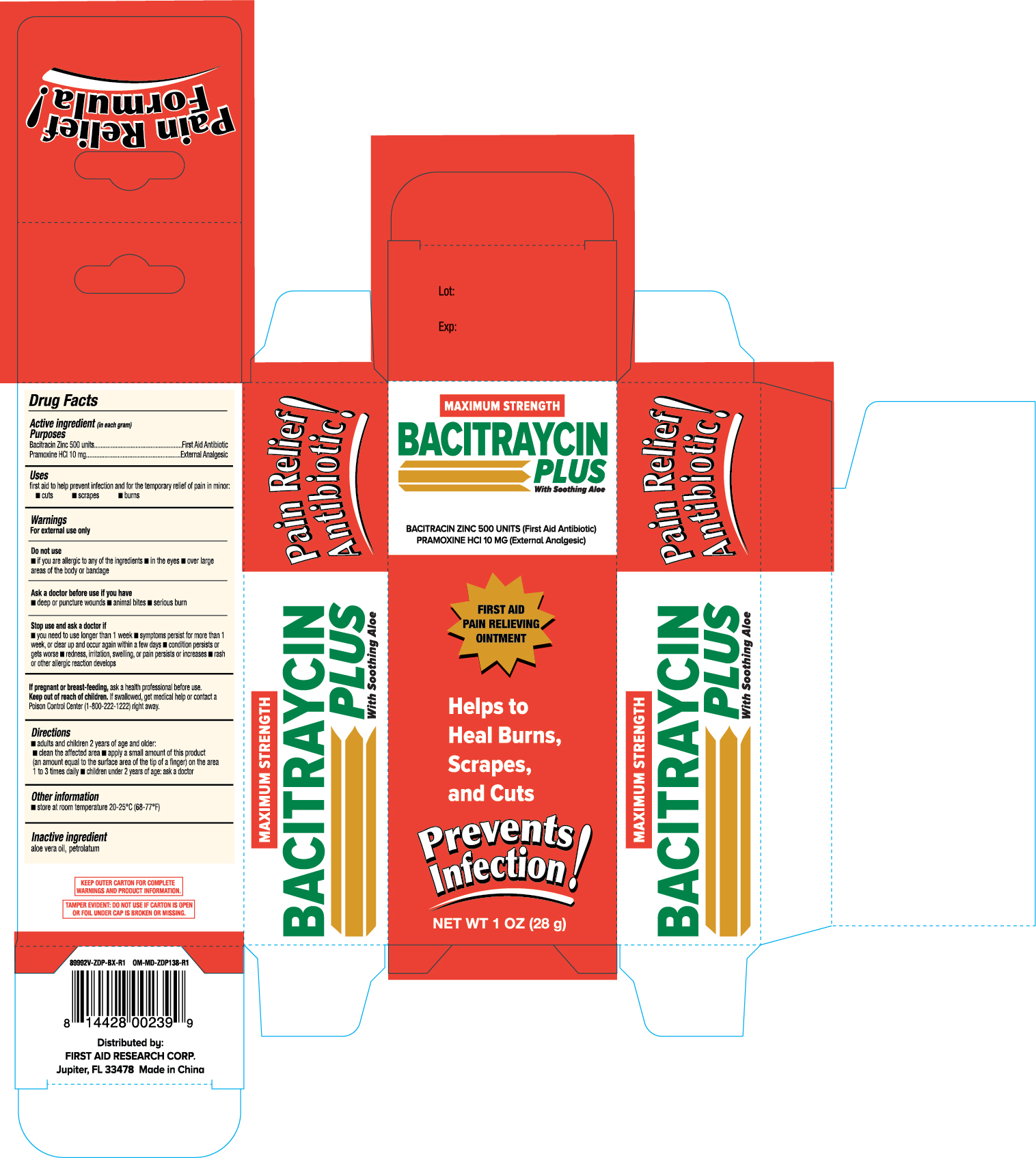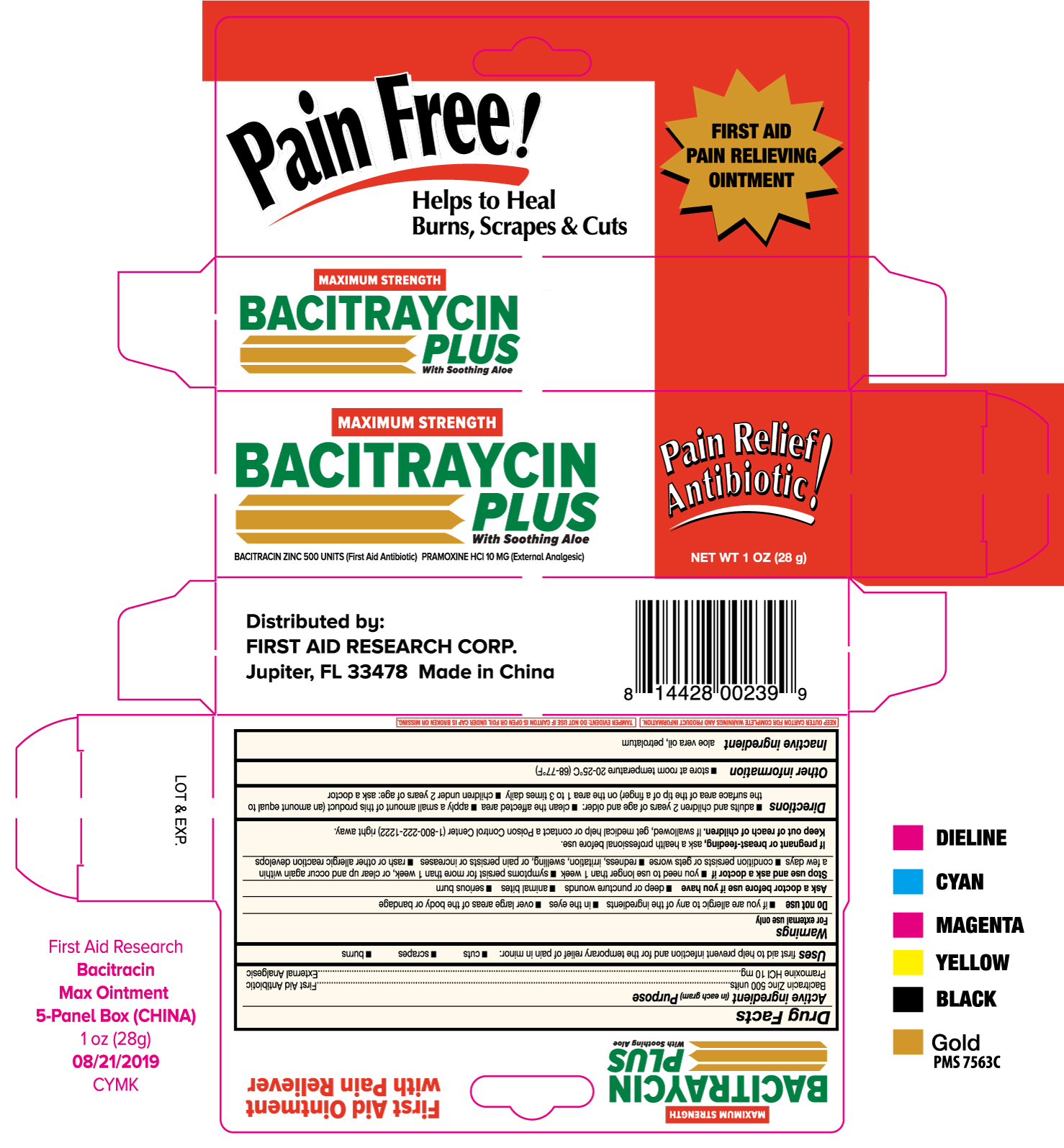 DRUG LABEL: bacitraycin plus
NDC: 75983-056 | Form: OINTMENT
Manufacturer: First Aid Research Corp
Category: otc | Type: HUMAN OTC DRUG LABEL
Date: 20201008

ACTIVE INGREDIENTS: PRAMOXINE HYDROCHLORIDE 10 mg/1 g; BACITRACIN ZINC 500 [USP'U]/1 g
INACTIVE INGREDIENTS: ALOE VERA LEAF; METHYLPARABEN; PETROLATUM; PROPYLPARABEN; STEARYL ALCOHOL; LIGHT MINERAL OIL

First Aid Research Max Strength Bacitraycin Plus Ointment 1oz w/ Pramoxine HCl Vertical (89992V, 2019)

Active ingredients (in each gram) Purposes

Bacitracin zinc 500 units............First aid antibiotic

Parmoxine HCl 10 mg...............External analgesic

Uses

- first aid to help prevent infection and for the temporary relief of pain in minor:
- cuts
- scrapes
- burns

WARNINGS

For external use only

Do no use

- if you are allergic to any of the ingredients
- in the eyes
- over large areas of the body or bandage

Ask a doctor before use if you have

- deep or puncture wounds
- animal bites
- serious burns

Stop use and ask a doctor if

- you need to use longer than 1 week
- symptoms persist for more than 1 week, or clear up and occur again within a few days
- condition persists or gets worse
- redness, irritation, swelling, or pain persists or increases
- rash or other allergic reactin develops

PREGNANCY OR BREAST FEEDING

If pregnant or breast-feeding, ask a health professional before use.

Keep out of reach of children. If swallowed, get medical help or contact a Poison Control Center (1-800-222-1222) right away.

Directions

- adults and children 2 years of age and older:
- clean the affected area
- apply a small amount of this product (an amount equal to the surface area of the tip of a finger) on the area 1 to 3 times daily
- children under 2 years of age: ask a doctor

Other information

- store at room temperature 20-25°C (68-77°F)

Inactive ingredients aloe vera oil, petrolatum

DOSAGE AND ADMINISTRATION

Dirtributed by:

FIRST AID RESEARCH CORP.

Jupiter, FL 33478 Made in China